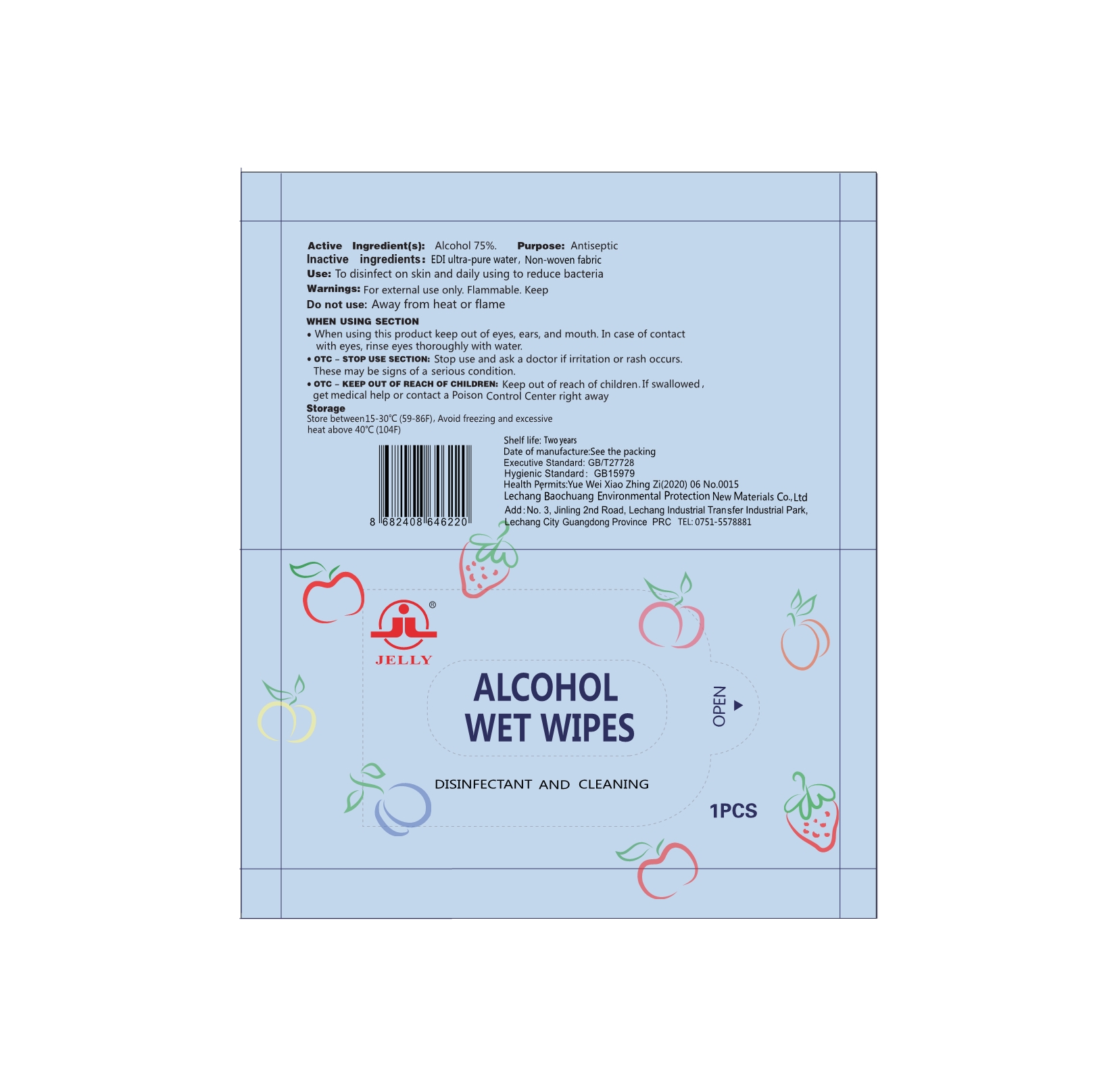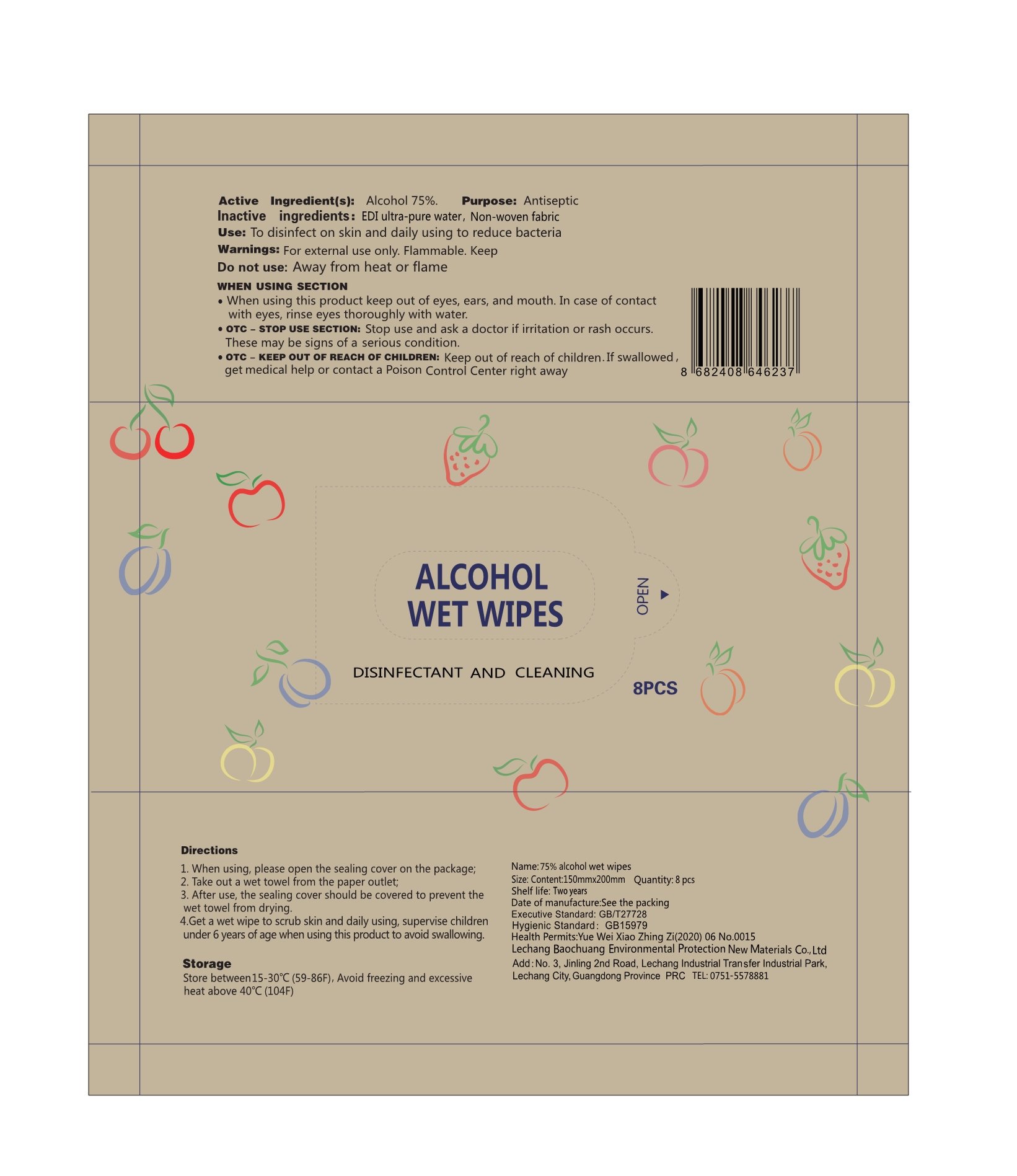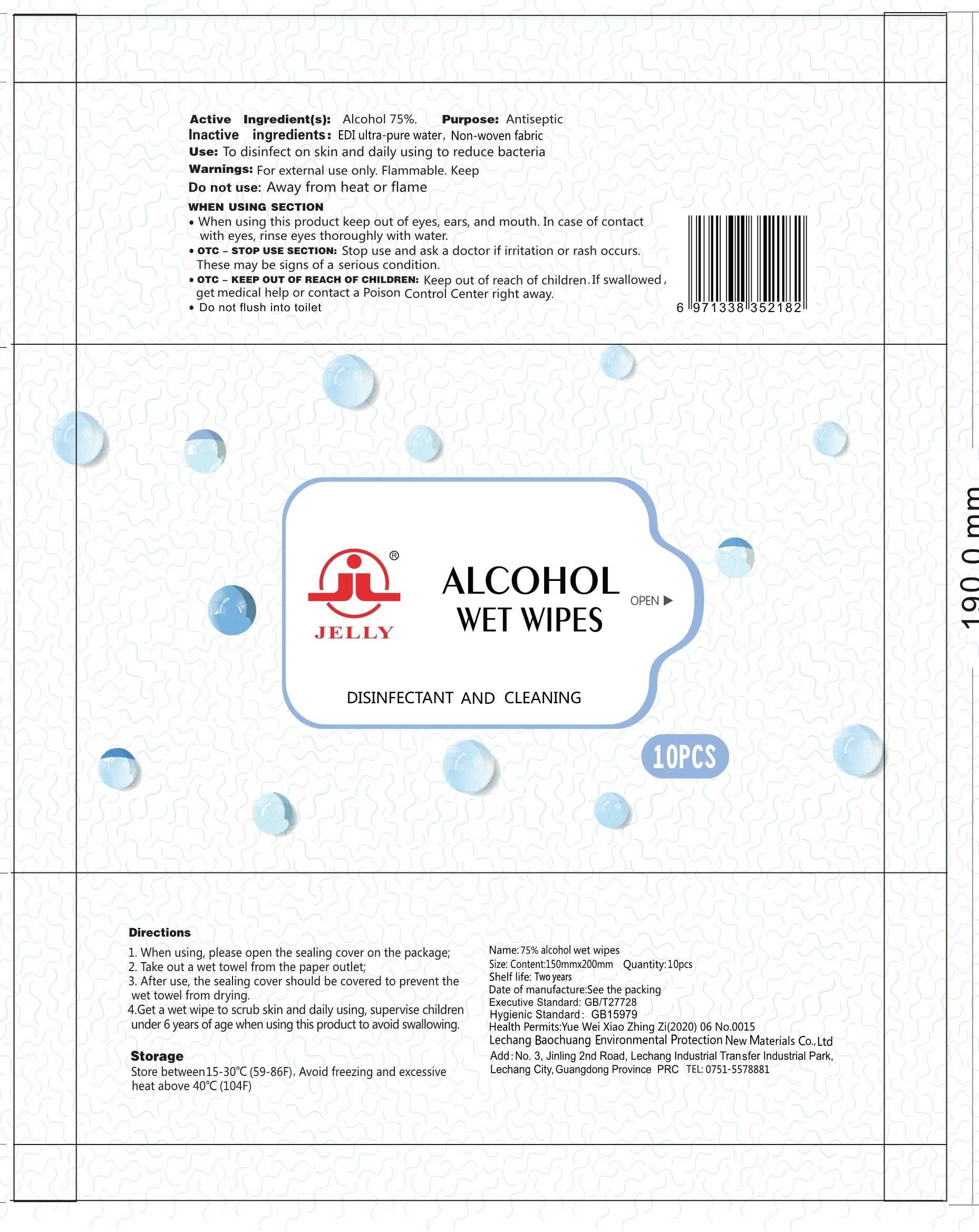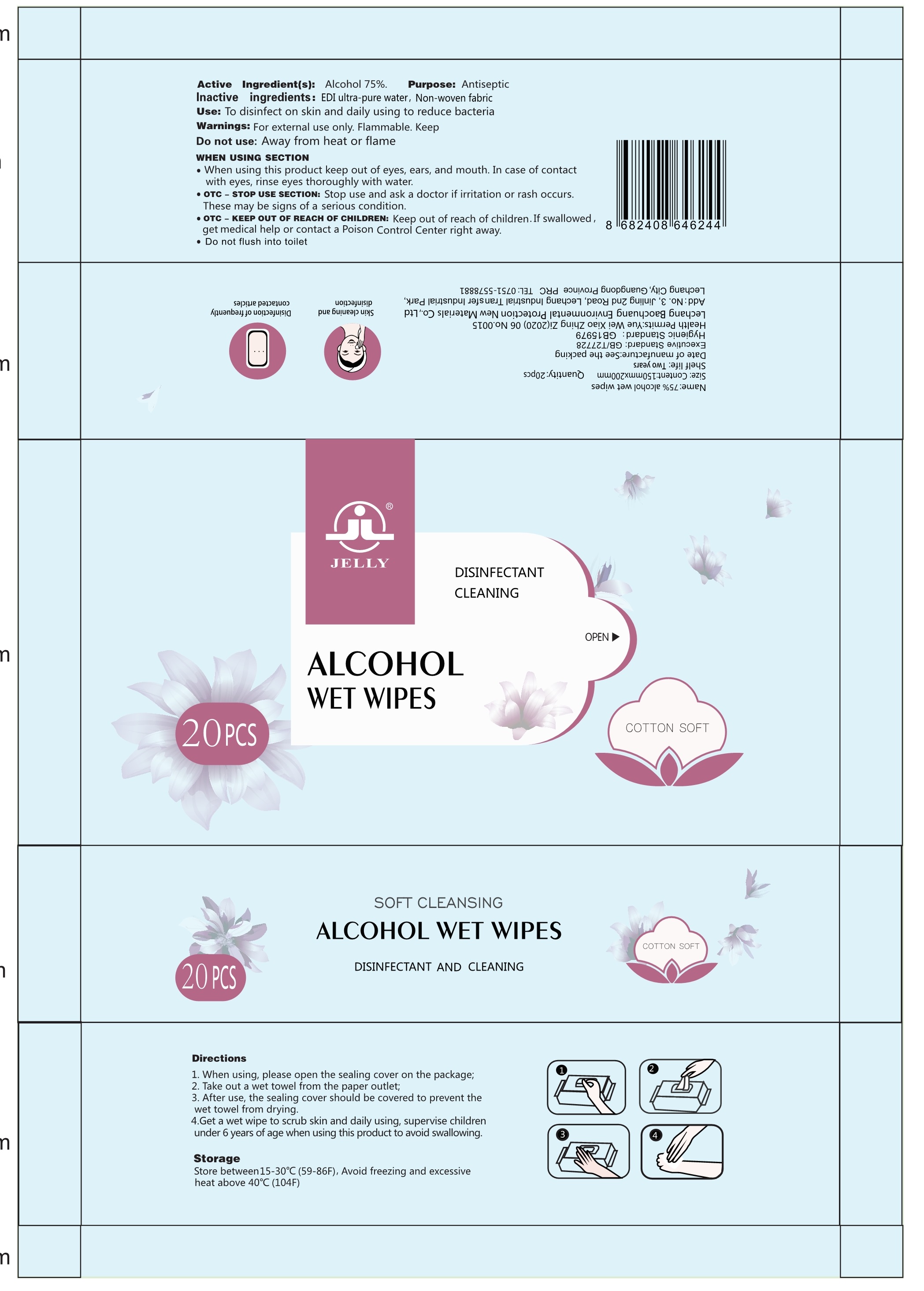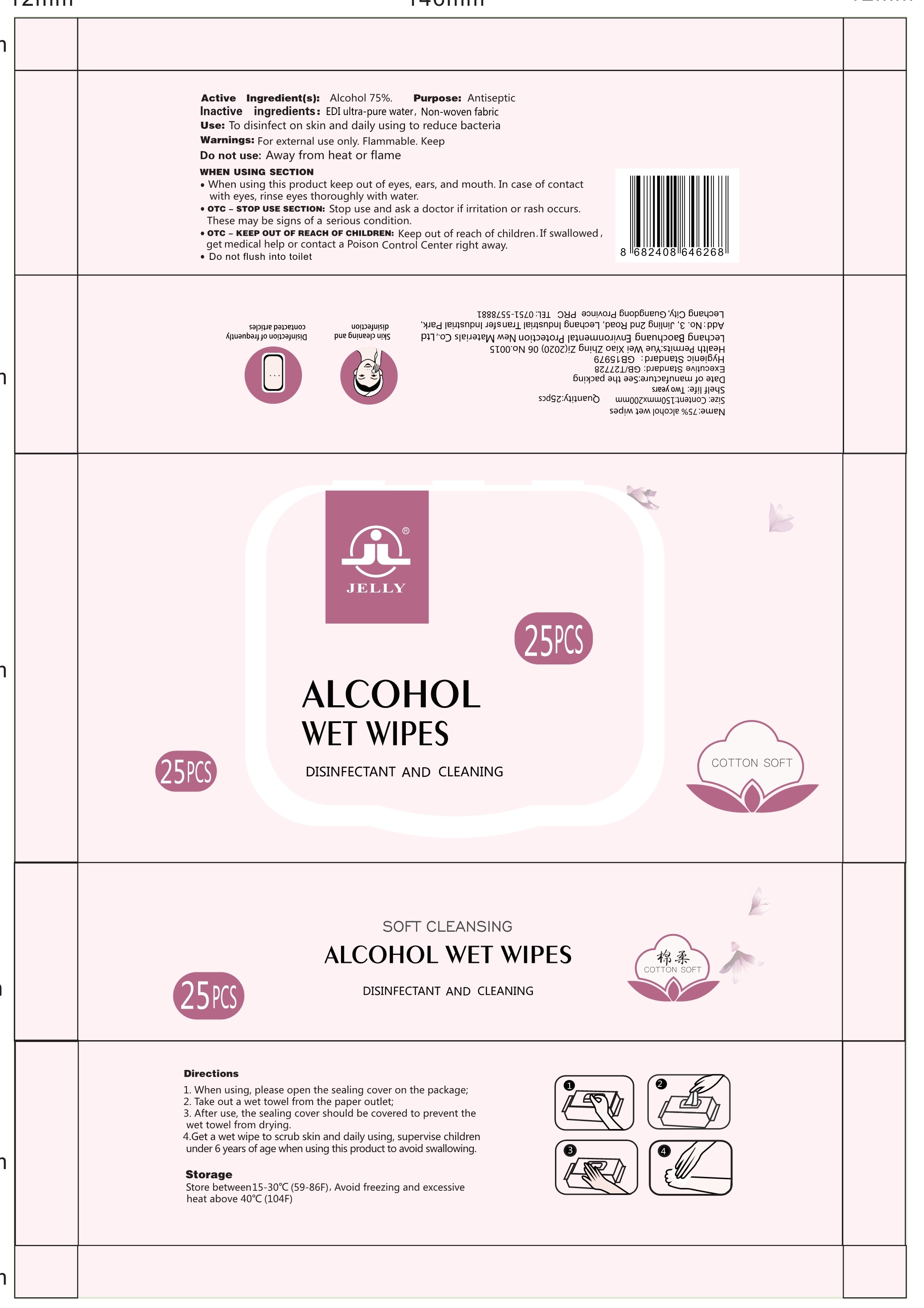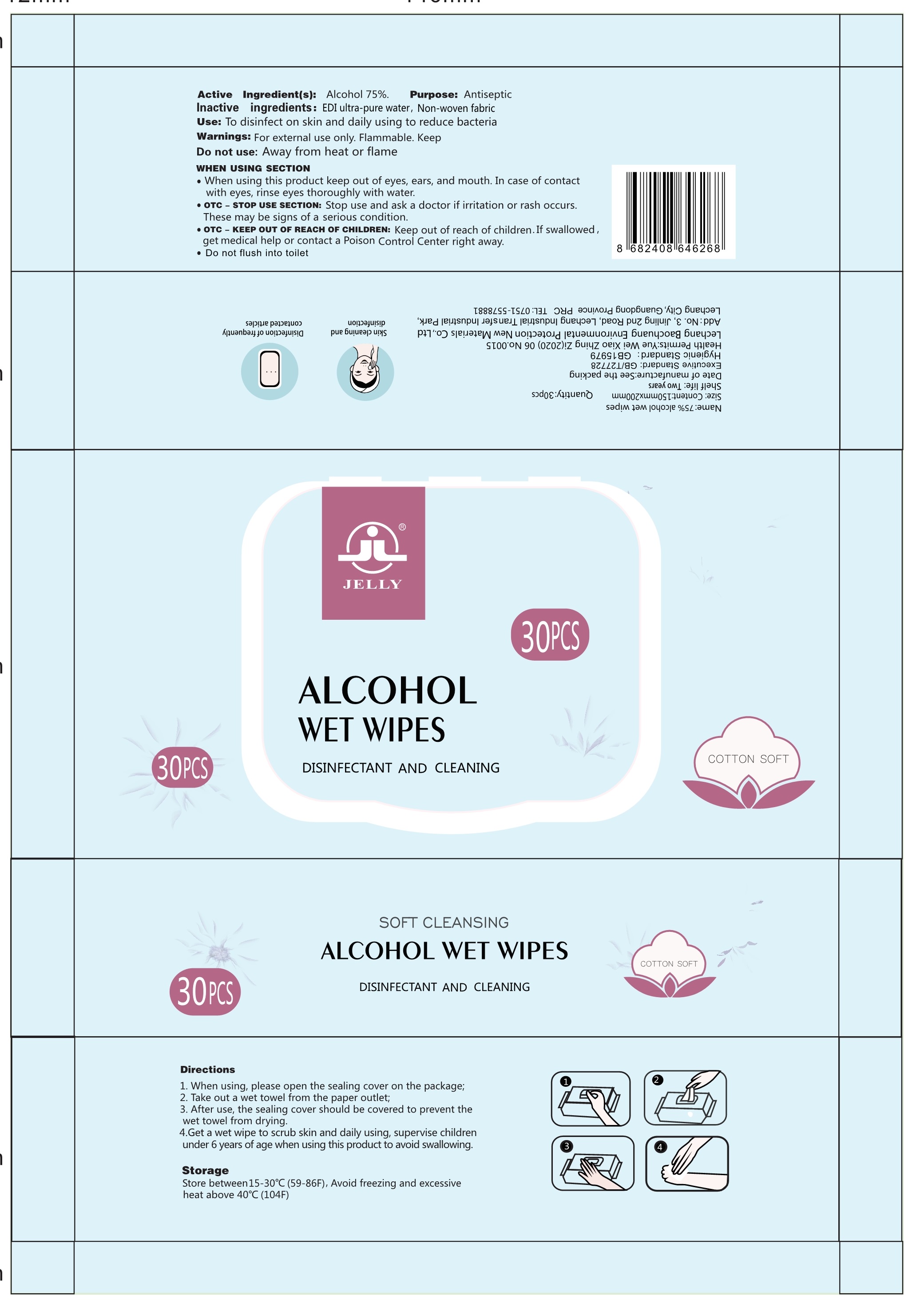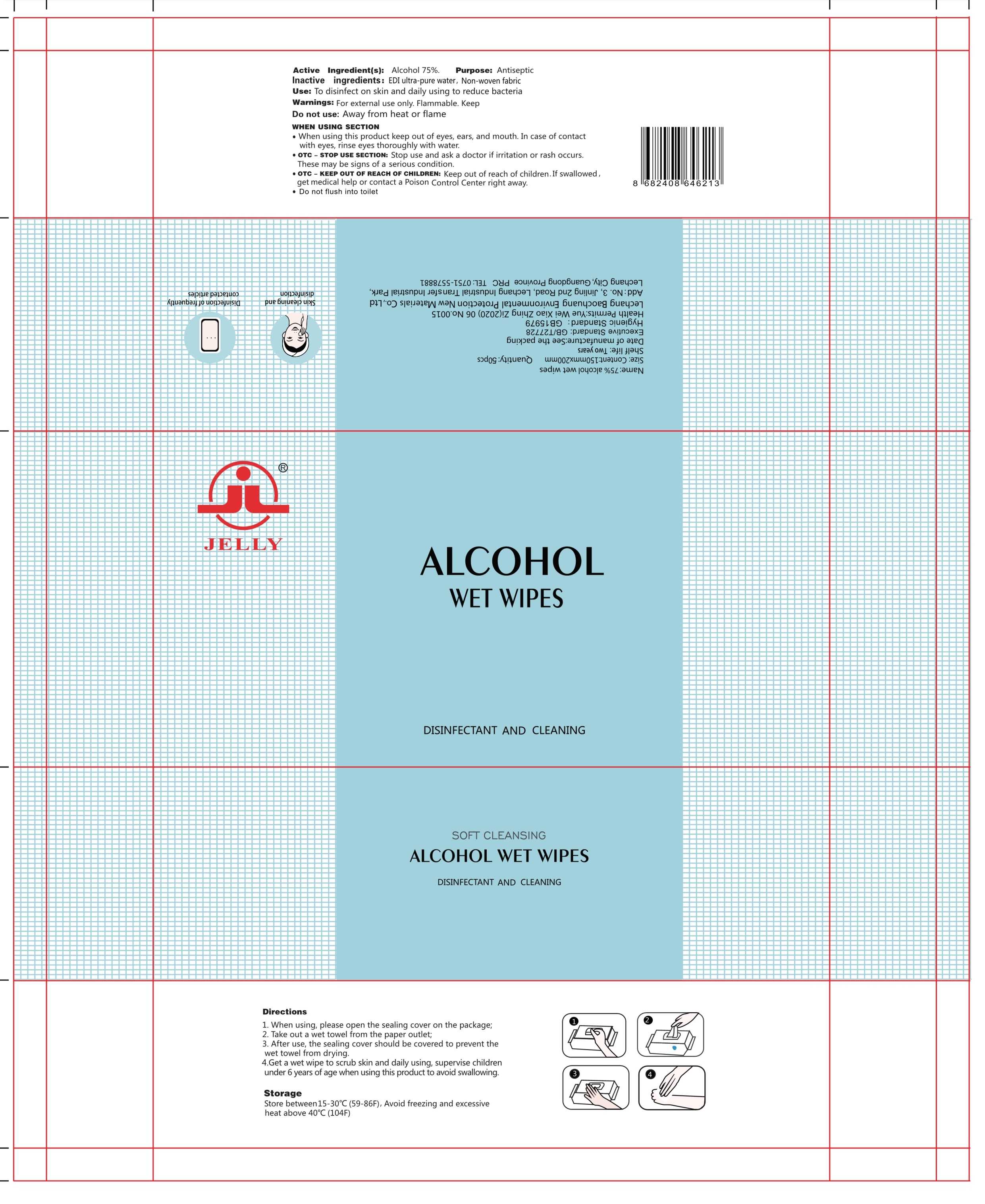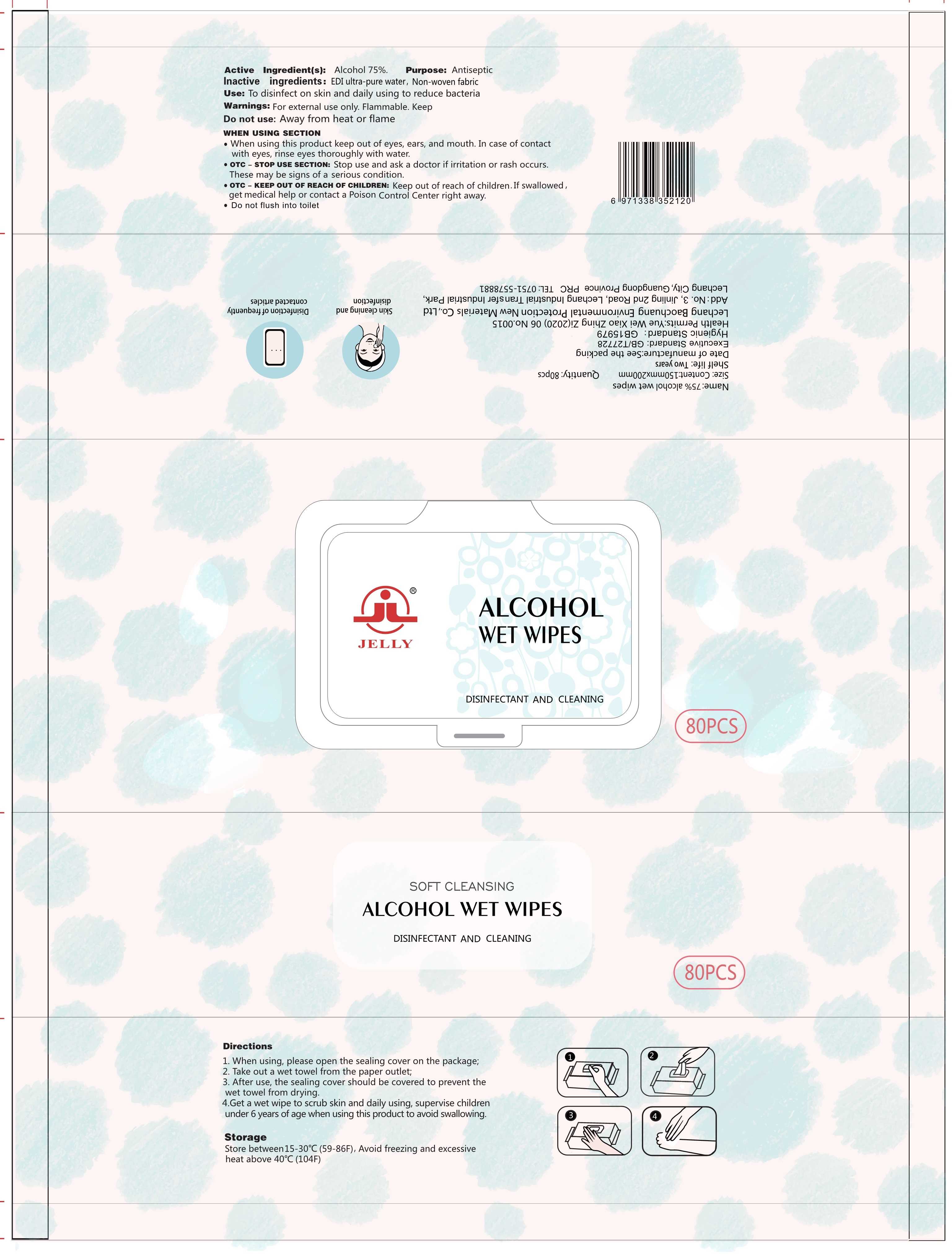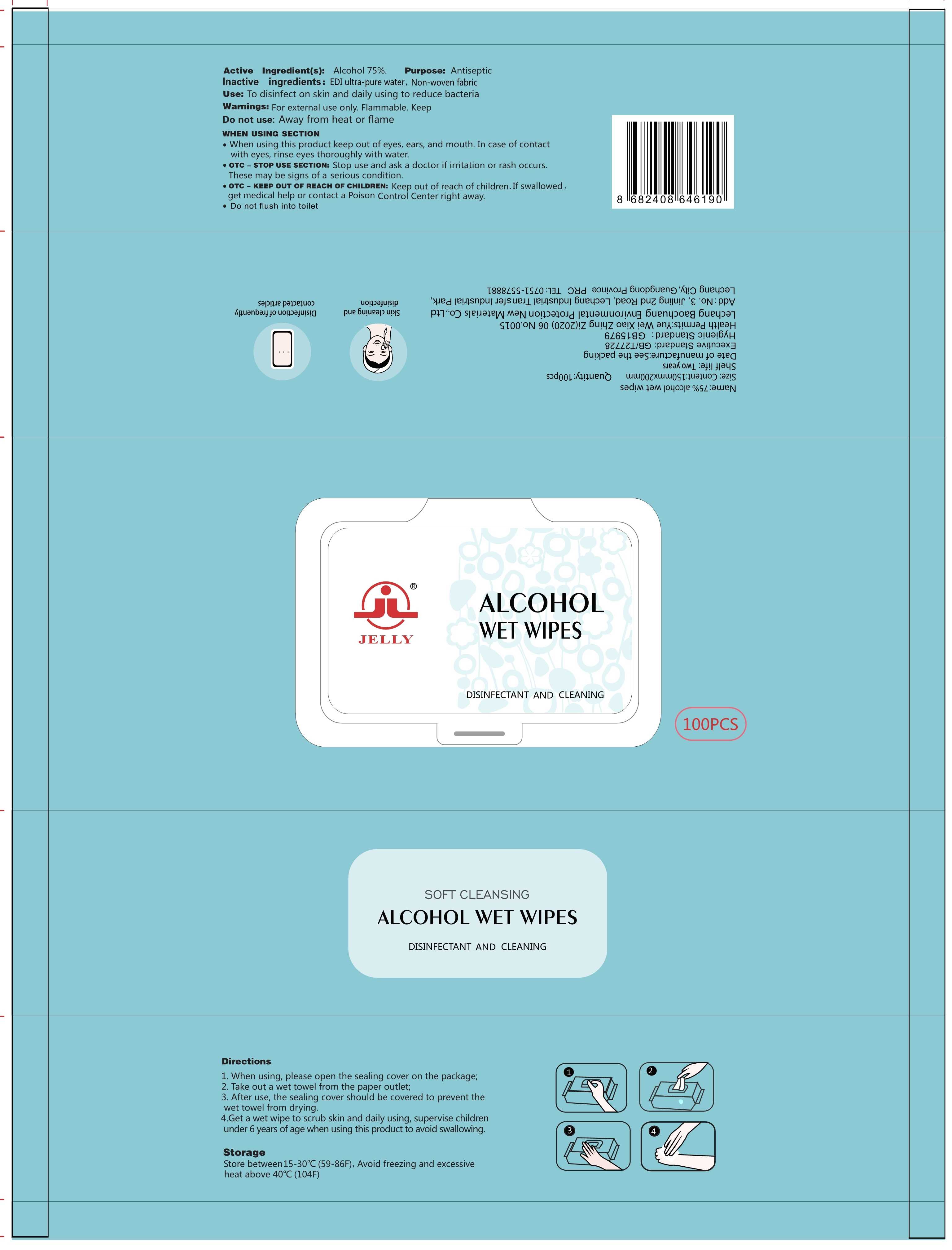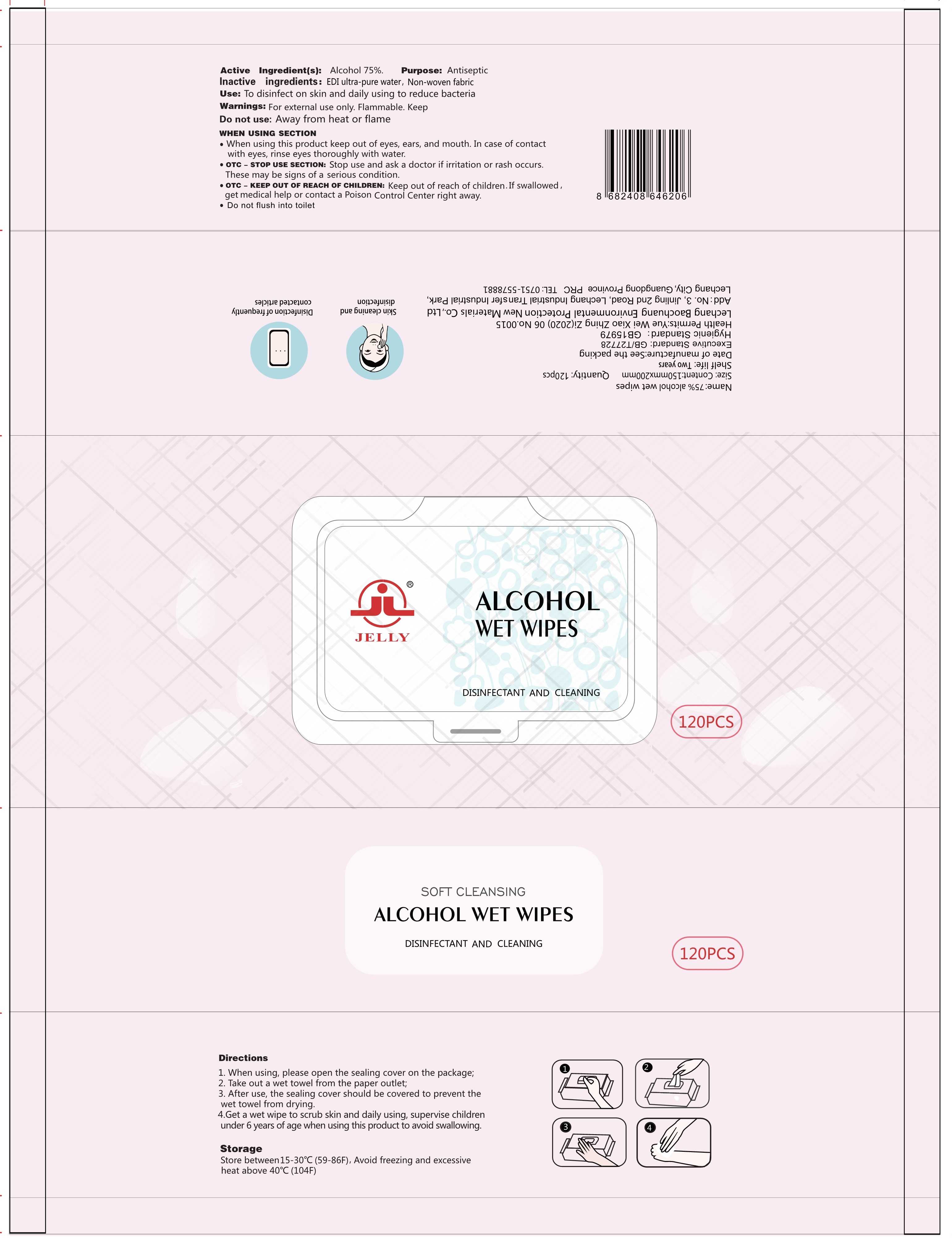 DRUG LABEL: 75% alcohol wet wipes
NDC: 79758-001 | Form: CLOTH
Manufacturer: LECHANG BAOCHUANG ENVIRONMENTAL PROTECTION NEW MATERIALS CO.,LTD.
Category: otc | Type: HUMAN OTC DRUG LABEL
Date: 20210226

ACTIVE INGREDIENTS: ALCOHOL 75 mL/100 1
INACTIVE INGREDIENTS: WATER

79758-001
75% alcohol wet wipes

Active Ingredient(s)

Alcohol 75%.

Purpose

Antiseptic

Use

To disinfect on skin and daily
using to reduce bacteria

Warnings

For external use only. Flammable. Keep

Do not use

Away from heat or flame

When using this product keep out of eyes, ears, and mouth. In case of contact with eyes, rinse eyes thoroughly with water

Stop use and ask a doctor if irritation or rash occurs.
These may be signs of a serious condition.

Keep out of reach of children. If swallowed , get
medical help or contact a Poison Control Center right away

Directions

1. When using, please open the sealing cover on the package;
2. Take out a wet towel from the paper outlet;
3. After use, the sealing cover should be covered to prevent the wet towel from drying.
4.Get a wet wipe to scrub skin and daily using, supervise children under 6 years of age when using this product to avoid swallowing.

Other information

Store between15-30℃ (59-86f)，Avoid freezing and excessive heat above 40℃（104F)

Inactive ingredients

EDI ultra-pure water, Non-woven fabric

Package Label - Principal Display Panel

79758-001-01 1P

79758-001-02 8P

79758-001-03 10P

79758-001-04 20P

79758-001-05 25P

79758-001-06 30P

79758-001-07 50P

79758-001-08 80P

79758-001-09 100p

79758-001-10 120p